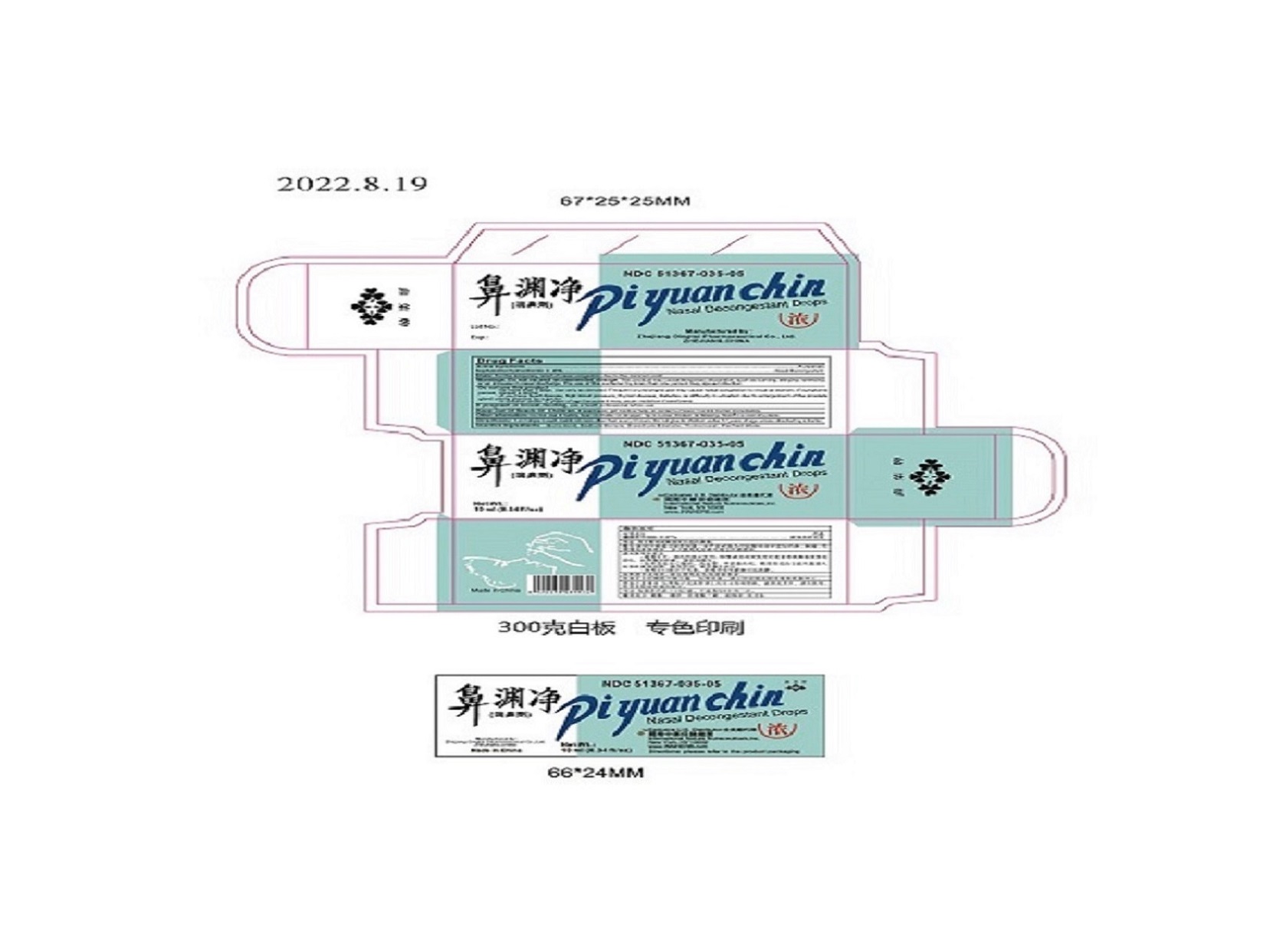 DRUG LABEL: Pi Yuan Chin
NDC: 51367-035 | Form: SOLUTION/ DROPS
Manufacturer: International Nature Nutraceuticals
Category: otc | Type: HUMAN OTC DRUG LABEL
Date: 20251227

ACTIVE INGREDIENTS: NAPHAZOLINE HYDROCHLORIDE 1 mg/1 1
INACTIVE INGREDIENTS: BORIC ACID; SODIUM BORATE; EDETATE DISODIUM; THIMEROSAL; WATER

Drug Facts

Active Ingredients

Naphazoline Hydrochloride: 0.05%

Purposes: Nasal Decongestant

Uses:

For the temporary relief of nasal congestion due to the common cold.

Warnings: Do not exceed recommended dosage.

This product may cause temporary discomfort such as burning, stinging, sneezing, or an increase in nasal discharge.

The use of this container by more than one person may spread infection.

Do not use this product

- for more than 3 days. Use only as directed. Frequent or prolonged use may cuase nasal congestion to recur or worsen. If symptons persist, consult a doctor.

- If you have heart disease, high blood pressure, thyroid disease, diabetes, or difficulty in urination due to enlargement of the prostate gland unless directed by a doctor.

- in children under 12 years of age because it may cause sedation if swallowed.

If pregnant or breast-feeding,

ask a health professional before use.

Keep Out Of Reach Of Children

If swallowed, get medical help, or contact a Poison Control Center immediately.

Other information:

Do not use if safety seal on bottle or dropper tip is loose, broken or missing. Store in a cool dry place.

Directions:

1 or 2 drops in each nostril not more often than every 6 hours.

Do not give to children under 12 years of age unless directed by a doctor.

Inactive Ingredients:

Boric Acid, Sodium Borate, Disodium Edetate, Thimerosal, Purified Water